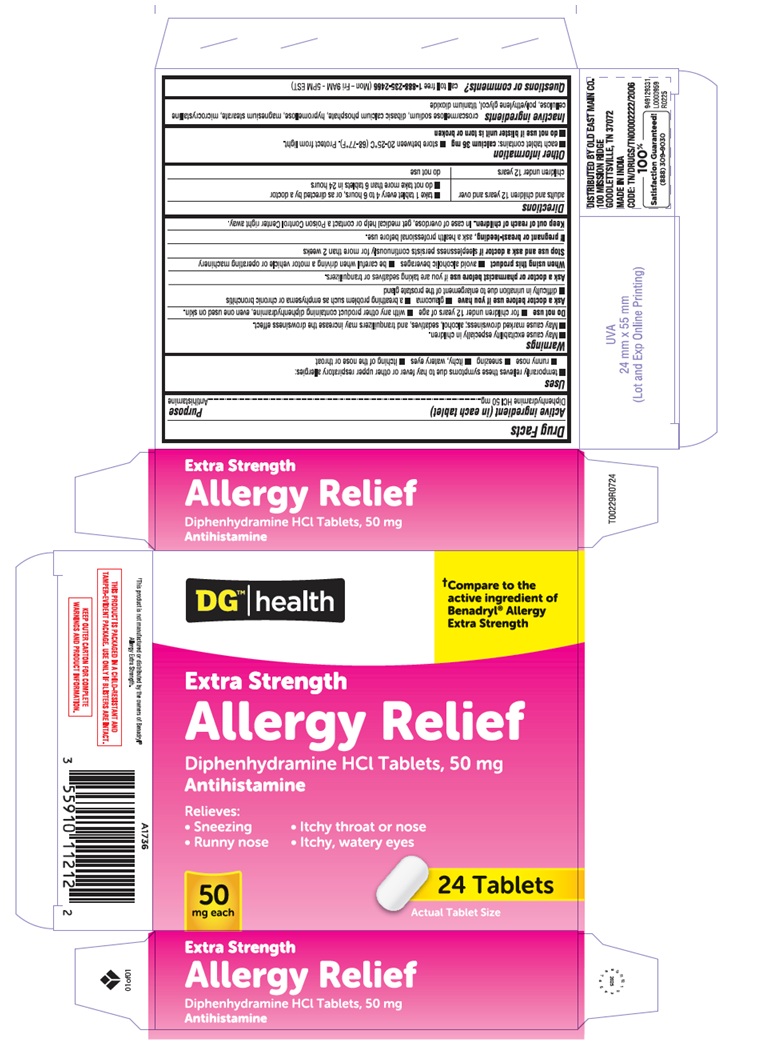 DRUG LABEL: Allergy Relief
NDC: 55910-450 | Form: TABLET
Manufacturer: DOLGENCORP INC
Category: otc | Type: HUMAN OTC DRUG LABEL
Date: 20250623

ACTIVE INGREDIENTS: DIPHENHYDRAMINE HYDROCHLORIDE 50 mg/1 1
INACTIVE INGREDIENTS: TITANIUM DIOXIDE; CROSCARMELLOSE SODIUM; ANHYDROUS DIBASIC CALCIUM PHOSPHATE; HYPROMELLOSE, UNSPECIFIED; MAGNESIUM STEARATE; MICROCRYSTALLINE CELLULOSE; POLYETHYLENE GLYCOL, UNSPECIFIED

Diphenhydramine HCl 50 mg tablet, Dollar General, allergy relief

Active ingredient (in each capsule)

Diphenhydramine HCl 50 mg

Purpose

Antihistamine

Uses

■ temporarily relieves these symptoms due to hay fever or the other upper respiratory allergies:
■ runny nose ■ sneezing ■ itchy, watery eyes ■ itching of the nose or throat

Warnings

■ May cause excitability especially in children.

■ May cause marked drowsiness; alcohol, sedatives, and tranquilizres may increase the drowsiness effect.

Do not use

■ for children under 12 years of age ■ with any other product containing diphenhydramine, even one used on skin.

Ask a doctor before use if you have

■ glaucoma ■ a breathing problem such as emphysema or chronic bronchitis
■ trouble urinating due to an enlarged prostate gland

Ask a doctor or pharmacist before use

if you are taking sedatives or tranquilizers.

When using this product

■ avoid alcoholic beverages ■ be careful when driving a motor vehicle or operating machinery

Stop use and ask a doctor if

sleeplessness persists continuously for more than 2 weeks

If pregnant or breast- feeding,

ask a health professional before use.

Keep out of reach of children.

In case of overdose, get medical help or contact a Poison Control Centre right away.

Directions

adults and children 12 years and over | ■ take 1 tablet every 4 to 6 hours, or as directed by a doctor; ■ do not take more than 6 tablets in 24 hours
children under 12 years | do not use

Other information

■ each tablet contains: calcium 36 mg ■ store between 20-25°C (68-77°F). Protect from light.

■ do not use if blister unit is torn or broken

Inactive ingredients

croscarmellose sodium, dibasic calcium phosphate, hypromellose, magnesium stearate, microcrystalline cellulose, polyethylene glycol, titanium dioxide

Questions or comments?

call toll-free 1-888-235-2466 (Mon - Fri 9AM - 5PM EST)

†This product is not manufactured or distributed by the owners of Benadryl® Allergy Extra Strength.

THIS PRODUCT IS PACKAGED IN A CHILD-RESISTANT AND

TAMPER-EVIDENT PACKAGE. USE ONLY IF BLISTERS ARE INTACT.

KEEP OUTER CARTON FOR COMPLETE

WARNINGS AND PRODUCT INFORMATION.

DISTRIBUTED BY OLD EAST MAIN CO.

100 MISSION RIDGE GOODLETTSVILLE, TN 37072

MADE IN INDIA

CODE: TN/DRUGS/TN00002222/2006

100%

Satisfaction Guaranteed!

(888) 309-9030

949129331

L0000959

R0225

carton

†Compare to the

active ingredient of
Benadryl® Allergy

Extra Strength

DGTM health

Extra Strength

Allergy Relief

diphenhydramine HCl Tablets, 50 mg
Antihistamine

Relieves:
• Sneezing • Itchy throat or nose
• Runny nose • Itchy, watery eyes

50

mg each

24 Tablets